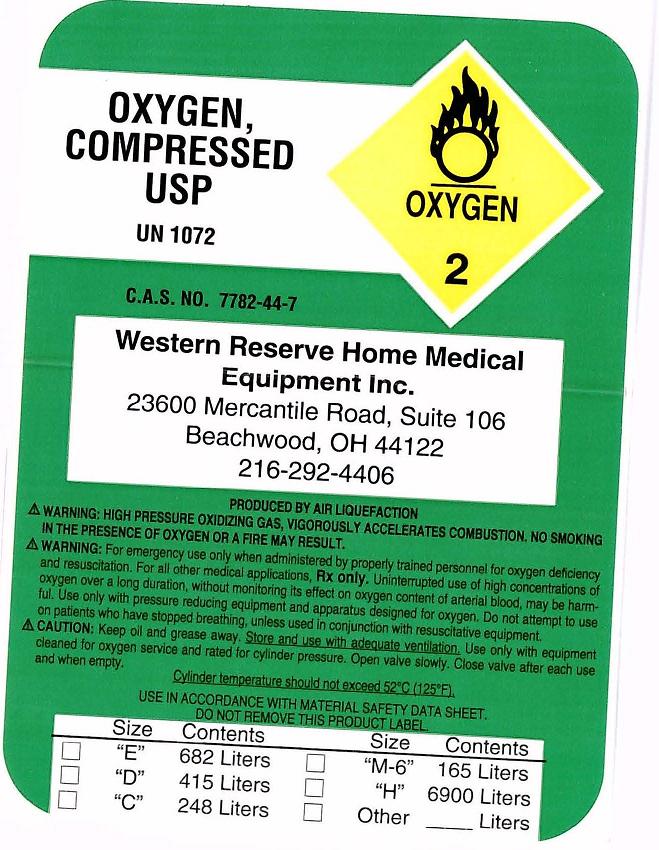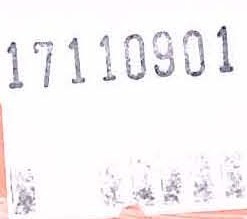 DRUG LABEL: Oxygen
NDC: 68899-0001 | Form: GAS
Manufacturer: Western Reserve Home Medical Eq.
Category: prescription | Type: HUMAN PRESCRIPTION DRUG LABEL
Date: 20091120

ACTIVE INGREDIENTS: Oxygen 99 L/100 L

Oxygen